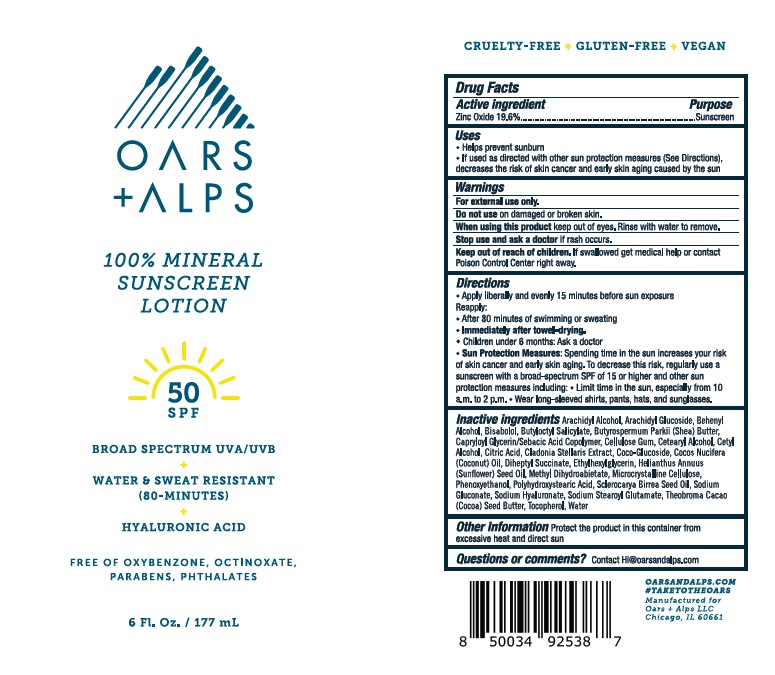 DRUG LABEL: Oars and Alps SPF 50 Mineral
NDC: 83046-371 | Form: LOTION
Manufacturer: Oars and Alps LLC
Category: otc | Type: HUMAN OTC DRUG LABEL
Date: 20241220

ACTIVE INGREDIENTS: ZINC OXIDE 19.6 g/100 mL
INACTIVE INGREDIENTS: METHYL DIHYDROABIETATE; SODIUM GLUCONATE; CARBOXYMETHYLCELLULOSE SODIUM, UNSPECIFIED; CETOSTEARYL ALCOHOL; CITRIC ACID MONOHYDRATE; ETHYLHEXYLGLYCERIN; POLYHYDROXYSTEARIC ACID (2300 MW); CLADONIA RANGIFERINA WHOLE; SUNFLOWER OIL; COCOA BUTTER; SHEA BUTTER; PHENOXYETHANOL; LEVOMENOL; ARACHIDYL ALCOHOL; ARACHIDYL GLUCOSIDE; DOCOSANOL; BUTYLOCTYL SALICYLATE; CAPRYLOYL GLYCERIN/SEBACIC ACID COPOLYMER (2000 MPA.S); WATER; CETYL ALCOHOL; COCONUT OIL; SCLEROCARYA BIRREA SEED OIL; TOCOPHEROL; MICROCRYSTALLINE CELLULOSE; HYALURONATE SODIUM; SODIUM STEAROYL GLUTAMATE; COCO GLUCOSIDE; DIHEPTYL SUCCINATE

Oars & Alps - SPF 50 Mineral Lotion

ACTIVE INGREDIENT

Zinc Oxide - 19.6%

PURPOSE

Sunscreen

Uses

• Helps prevent sunburn
• If used as directed with other sun protection measures (see Directions), decreases the risk of skin cancer and early skin aging caused by the sun.

WARNINGS

• For external use only.
• Do not use on damaged or broken skin.
• When using this product keep out of eyes. Rinse with water to remove.
• Stop use and ask a doctor if rash occurs.

Keep out of reach of children. If swallowed, get medical help or contact a Poison Control Center right away.

DOSAGE AND ADMINISTRATION

Apply liberally 15 minutes before sun exposure.

Reapply:

-At least every two hours
-After 80 minutes of swimming or sweating.
-Immediately after towel drying.
Children under six months: Ask a doctor.

Sun Protection Measures: Spending time in the sun increases your risk of skin cancer and early skin aging. To decrease this risk, regularly use a sunscreen with a Broad Spectrum SPF value of 15 or higher and other sun protection measures including: • Limit time in the sun especially from 10 a.m. – 2 p.m. • Wear long-sleeved shirts, pants, hats, and sunglasses.

INACTIVE INGREDIENT

Arachidyl Alcohol, Arachidyl Glucoside, Behenyl Alcohol, Bisabolol, Butyloctyl Salicylate, Butyrospermum Parkii (Shea) Butter, Capryloyl Glycerin/Sebacic Acid Copolymer, Cellulose Gum, Cetearyl Alcohol, Cetyl Alcohol, Citric Acid, Cladonia Stellaris Extract, Coco-Glucoside, Cocos Nucifera (Coconut) Oil, Diheptyl Succinate, Ethylhexylglycerin, Helianthus Annuus (Sunflower) Seed Oil, Methyl Dihydroabietate, Microcrystalline Cellulose, Phenoxyethanol, Polyhydroxystearic Acid, Sclerocarya Birrea Seed Oil, Sodium Gluconate, Sodium Hyaluronate, Sodium Stearoyl Glutamate, Theobroma Cacao (Cocoa) Seed Butter, Tocopherol, Water

OTHER SAFETY INFORMATION

Protect the product in this container from excessive heat and direct sun

QUESTIONS

Contact Hi@oarsandalps.com